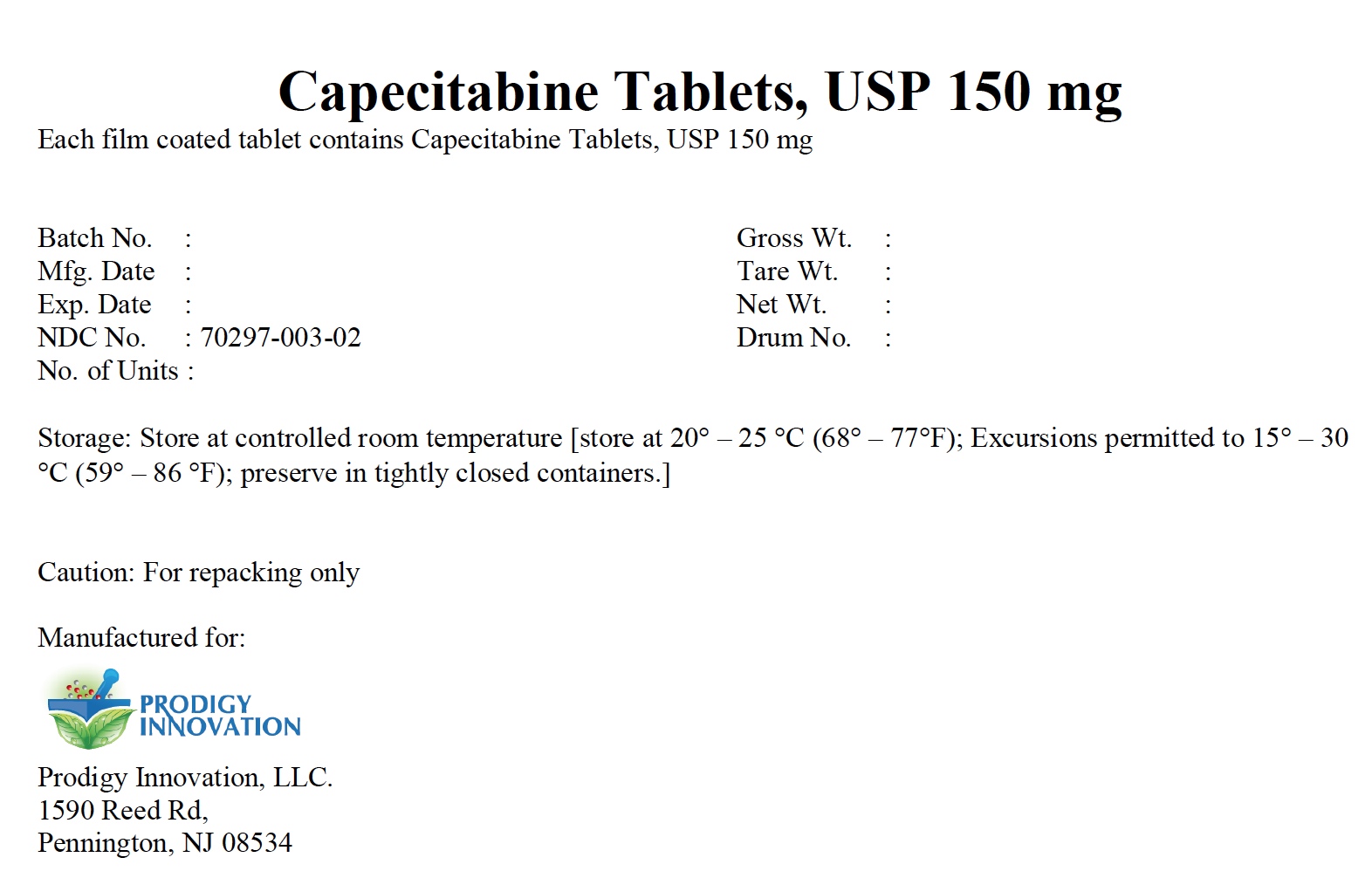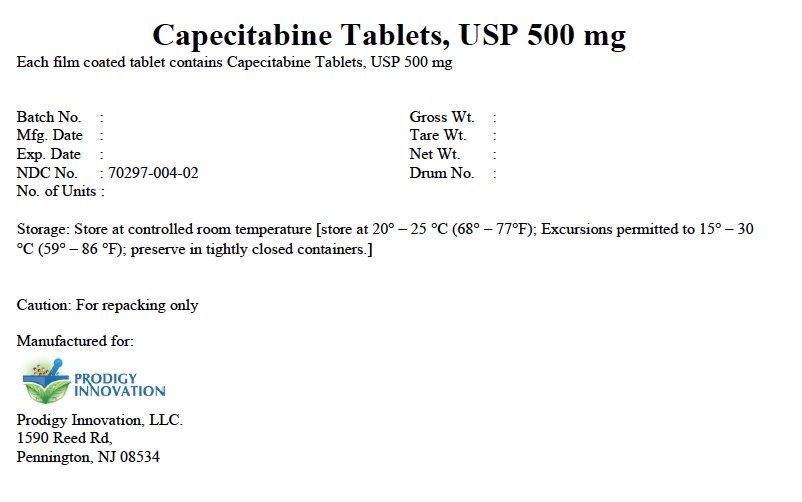 DRUG LABEL: Capecitabine Tablets, 150 mg
NDC: 70297-003 | Form: TABLET
Manufacturer: Prodigy Innovation, LLC.
Category: prescription | Type: HUMAN PRESCRIPTION DRUG LABEL
Date: 20190421

ACTIVE INGREDIENTS: CAPECITABINE 150 mg/1 1
INACTIVE INGREDIENTS: MICROCRYSTALLINE CELLULOSE 102; LACTOSE MONOHYDRATE; CROSCARMELLOSE SODIUM; MAGNESIUM STEARATE

Capecitabine Tablets, USP 150 mg and 500 mg